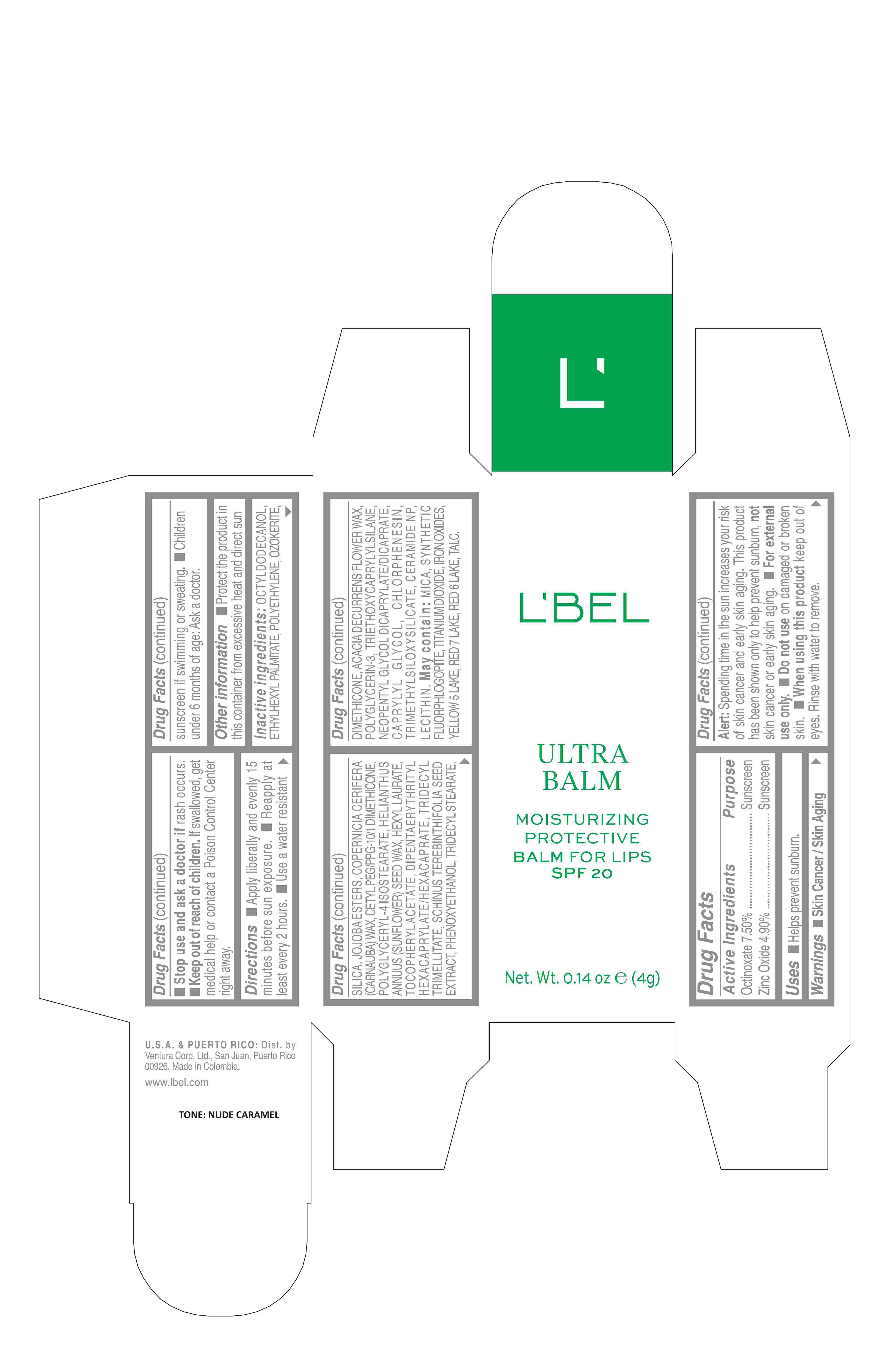 DRUG LABEL: Ultra Balm Moisturizing Protective Balm for lips SPF 20 Nude Caramel
NDC: 14141-457 | Form: STICK
Manufacturer: BEL STAR S A
Category: otc | Type: HUMAN OTC DRUG LABEL
Date: 20250619

ACTIVE INGREDIENTS: OCTINOXATE 7.5 g/100 g; ZINC OXIDE 4.9 g/100 g
INACTIVE INGREDIENTS: CHLORPHENESIN; FERRIC OXIDE YELLOW; FERROSOFERRIC OXIDE; TRIMETHYLSILOXYSILICATE (M/Q 0.6-0.8); POLYGLYCERYL-4 ISOSTEARATE; TRIDECYL STEARATE; DIMETHICONE; LECITHIN, SOYBEAN; MICA; FERRIC OXIDE RED; TALC; CETYL PEG/PPG-10/1 DIMETHICONE (HLB 1.5); HELIANTHUS ANNUUS SEED WAX; HEXYL LAURATE; .ALPHA.-TOCOPHEROL ACETATE; BRAZILIAN PEPPER; PHENOXYETHANOL; ACACIA DECURRENS FLOWER WAX; MAGNESIUM POTASSIUM ALUMINOSILICATE FLUORIDE; DIPENTAERYTHRITYL HEXACAPRYLATE/HEXACAPRATE; TRIDECYL TRIMELLITATE; POLYGLYCERIN-3; TRIETHOXYCAPRYLYLSILANE; NEOPENTYL GLYCOL DICAPRYLATE/DICAPRATE; CAPRYLYL GLYCOL; CERAMIDE NP; TITANIUM DIOXIDE; ETHYLHEXYL PALMITATE; OCTYLDODECANOL; HIGH DENSITY POLYETHYLENE; CERESIN; SILICON DIOXIDE; CARNAUBA WAX

Ultra Balm Moisturizing Protective Balm for lips SPF 20

Active Ingredients Purpose

Octinoxate 7.50% Sunscreen

Zinc Oxide 4.90% Sunscreen

Uses

- Helps prevent sunburn.

Keep out of reach of children.If swallowed, get medical help or contact a Poison Control Center right away.

Stop use and ask a doctor ifrash occurs.

WARNINGS

Skin Cancer / Skin Aging Alert:Spending time in the sun increases your risk of skin cancer and early skin aging. This product has been shown only to help prevent sunburn, not skin cancer or early skin aging.
For external use only.
Do not useon damaged or broken skin.
When using this productkeep out of eyes. Rinse with water to remove.

Directions

- Apply liberally and evenly 15 minutes before sun exposure.
- Reapply at least every 2 hours
- Use a water resistant sunscreen if swimming or sweating.
- Children under 6 months of age: Ask a doctor

INACTIVE INGREDIENT

Inactive ingredients:octyldodecanol, ethylhexyl palmitate, polyethylene, ozokerite, silica, jojoba esters, copernicia cerifera (carnauba) wax, cetyl peg/ppg-10/1 dimethicone, polyglyceryl-4 isostearate, helianthus annuus (sunflower) seed wax, hexyl laurate, tocopheryl acetate, dipentaerythrityl hexacaprylate/hexacaprate, tridecyl trimellitate, schinus terebinthifolia seed extract, phenoxyethanol, tridecyl stearate, dimethicone, acacia decurrens flower wax, polyglycerin-3, triethoxycaprylylsilane, neopentyl glycol dicaprylate/dicaprate, caprylyl glycol, chlorphenesin, trimethylsiloxysilicate, ceramide np, lecithin.
may contain:
mica, titanium dioxide, synthetic fluorphlogopite, iron oxides, yellow 5 lake, red 7 lake, red 6 lake, talc.

Other information

- Protect the product in this container from excessive heat and direct sun